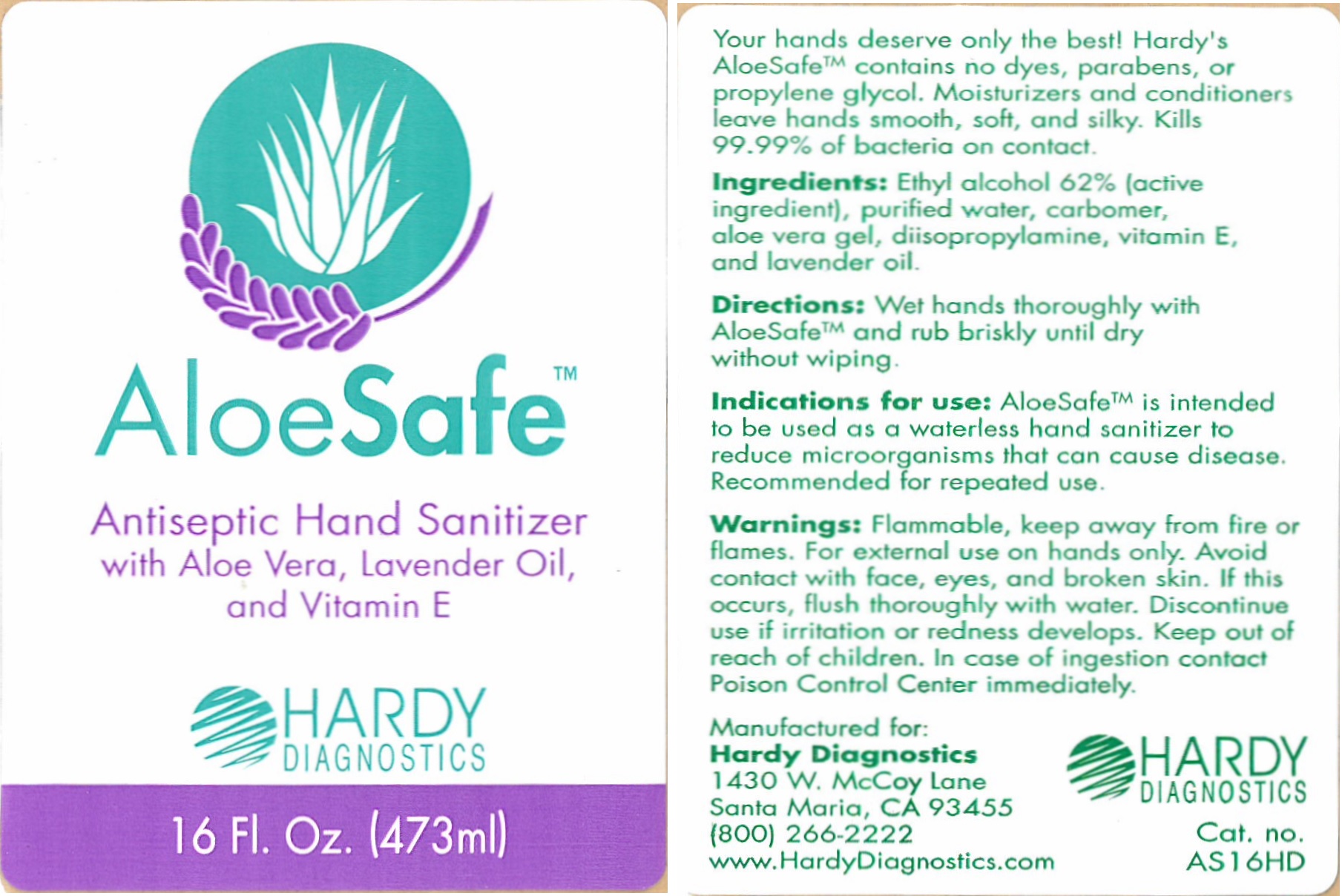 DRUG LABEL: AloeSafe
NDC: 12745-180 | Form: LIQUID
Manufacturer: Medical Chemical Corporation
Category: otc | Type: HUMAN OTC DRUG LABEL
Date: 20250731

ACTIVE INGREDIENTS: ALCOHOL 60 g/100 mL
INACTIVE INGREDIENTS: POLYACRYLIC ACID (450000 MW) 0.25 g/100 mL; ALOE VERA LEAF 0.2 g/100 mL; LAVENDER OIL 0.02 g/100 mL; ALPHA-TOCOPHEROL ACETATE 0.04 g/100 mL; WATER 28.03 g/100 mL; DIISOPROPYLAMINE 0.2 mL/100 mL

AloeSafe

Indications for use: AloeSafe is intended to be used as a waterless hand sanitizer to reduce microorganisms that can cause disease. Recommended fo repeated use.

Ingredients

Ingredients: Ethyl alcohol 62% (active ingredient), purified water, carbomer, aloe vera gel, diisopropylamine, vitamin E, and lavender oil.

Ingredients

Ingredients: Ethyl alcohol 62% (active ingredient), purified water, carbomer, aloe vera gel, diisopropylamine, vitamin E, and lavender oil.

Warnings

Warnings: Flammable, keep away from fire or flames. For external use on hands only. Avoid contact with face, eyes and broken skin. If this occurs, flush thoroughly with water. Discontinue use if irritation or redness develops. Keep out of reach of children. In case of ingestion contact Poison Control Center immediately.

Warnings

Warnings: Flammable, keep away from fire or flames. For external use on hands only. Avoid contact with face, eyes and broken skin. If this occurs, flush thoroughly with water. Discontinue use if irritation or redness develops. Keep out of reach of children. In case of ingestion contact Poison Control Center immediately.

Warnings

Warnings: Flammable, keep away from fire or flames. For external use on hands only. Avoid contact with face, eyes and broken skin. If this occurs, flush thoroughly with water. Discontinue use if irritation or redness develops. Keep out of reach of children. In case of ingestion contact Poison Control Center immediately.

Directions

Directions: Wet hands thoroughly with AloeSafe and rub briskly until dry without wiping.

Indications for use: AloeSafe is intended to be used as a waterless hand sanitizer to reduce microorganisms that can cause disease. Recommended fo repeated use.